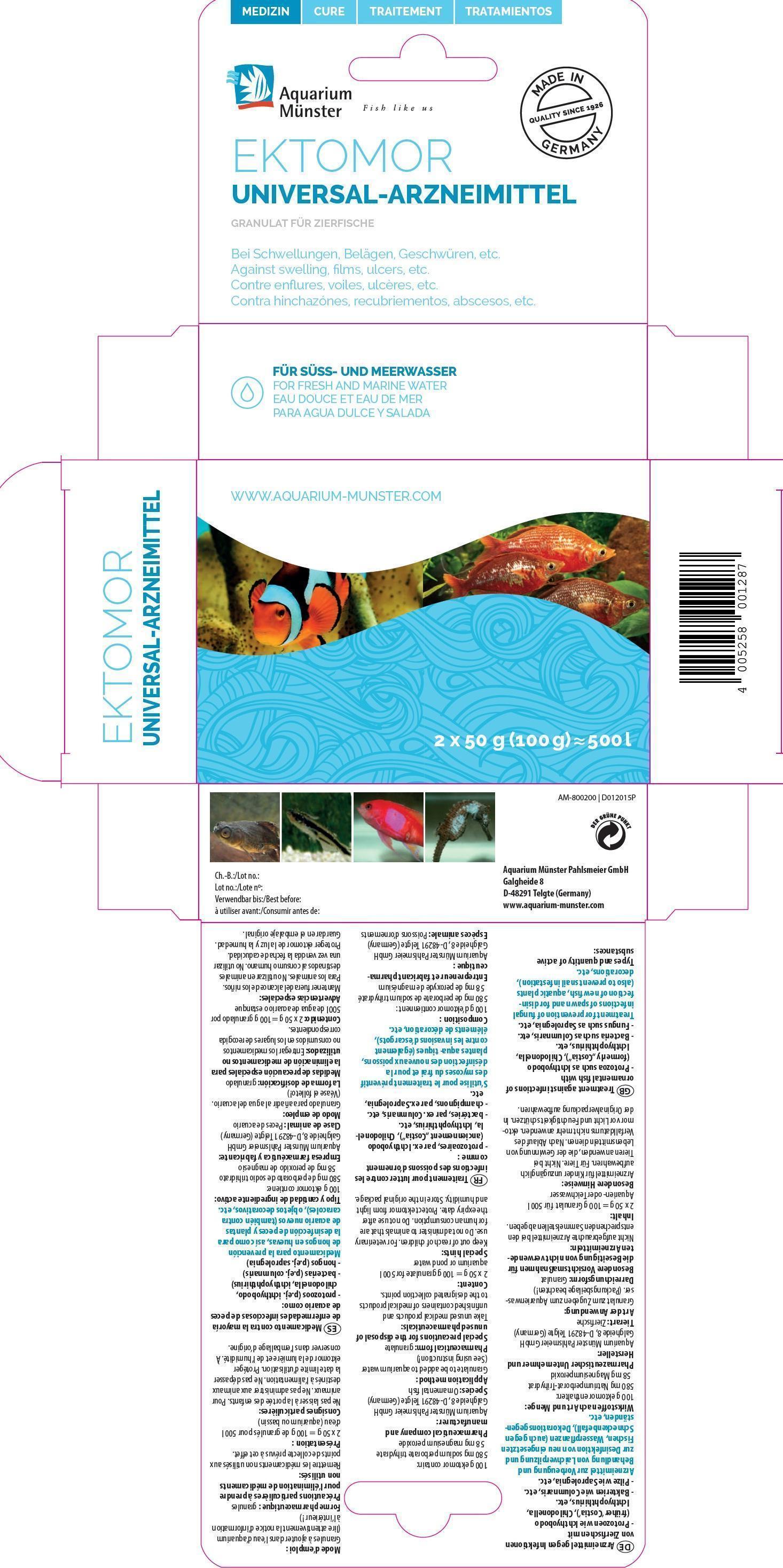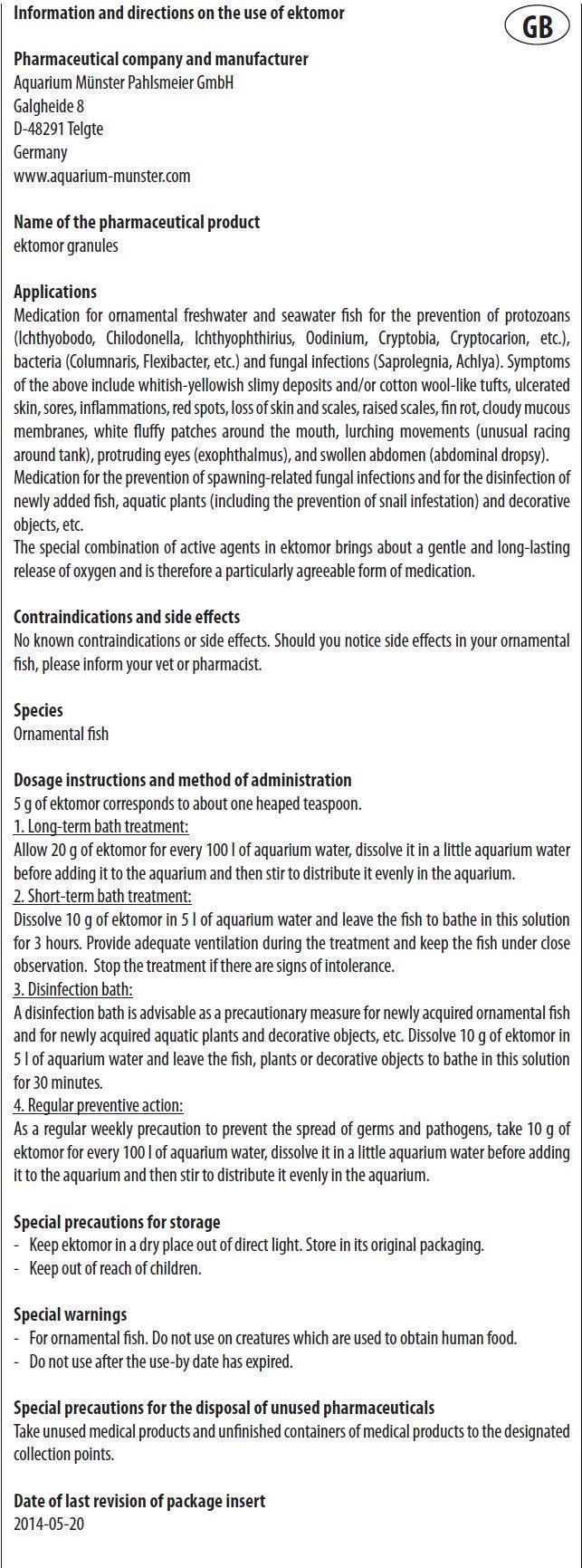 DRUG LABEL: Ektomor
NDC: 86052-006 | Form: GRANULE, FOR SOLUTION
Manufacturer: Aquarium Muenster Pahlsmeier GmbH
Category: animal | Type: OTC ANIMAL DRUG LABEL
Date: 20240419

ACTIVE INGREDIENTS: MAGNESIUM PEROXIDE 5.8 g/100 g

Ektomor

Information and directions on the use of ektomor

Pharmaceutical company and manufacturer
Aquarium Münster Pahlsmeier GmbH
Galgheide 8
D-48291 Telgte
Germany
www.aquarium-munster.com

Name of the pharmaceutical product
ektomor granules

Applications

Medication for ornamental freshwater and seawater fish for the prevention of protozoans (Ichthyobodo, Chilodonella, Ichthyophthirius, Oodinium, Cryptobia, Cryptocarion, etc.), bacteria (Columnaris, Flexibacter, etc.) and fungal infections (Saprolegnia, Achlya). Symptoms of the above include whitish-yellowish slimy deposits and/or cotton wool-like tufts, ulcerated skin, sores, inflammations, red spots, loss of skin and scales, raised scales, fin rot, cloudy mucous membranes, white fluffy patches around the mouth, lurching movements (unusual racing
around tank), protruding eyes (exophthalmus), and swollen abdomen (abdominal dropsy). Medication for the prevention of spawning- related fungal infections and for the disinfection of newly added fish, aquatic plants (including the prevention of snail infestation) and decorative objects, etc. The special combination of active agents in ektomor brings about a gentle and long-lasting release of oxygen and is therefore a particularly agreeable form of medication.

Types and quantity of active substances:

100 g ektomor contain:
580 mg sodium perborate trihydrate
58 mg magnesium peroxide

Contraindications and side effects

No known contraindications or side effects. Should you notice side effects in your ornamental fish, please inform your vet or pharmacist.

Species

Ornamental fish

Dosage instructions and method of administration

5 g of ektomor corresponds to about one heaped teaspoon.
1. Long-term bath treatment:
Allow 20 g of ektomor for every 100 l of aquarium water, dissolve it in a little aquarium water before adding it to the aquarium and then stir to distribute it evenly in the aquarium.
2. Short-term bath treatment:
Dissolve 10 g of ektomor in 5 l of aquarium water and leave the fish to bathe in this solution for 3 hours. Provide adequate ventilation during the treatment and keep the fish under close observation. Stop the treatment if there are signs of intolerance.
3. Disinfection bath:
A disinfection bath is advisable as a precautionary measure for newly acquired ornamental fish and for newly acquired aquatic plants and decorative objects, etc. Dissolve 10 g of ektomor in 5 l of aquarium water and leave the fish, plants or decorative objects to bathe in this solution
for 30 minutes.
4. Regular preventive action:
As a regular weekly precaution to prevent the spread of germs and pathogens, take 10 g of ektomor for every 100 l of aquarium water, dissolve it in a little aquarium water before adding it to the aquarium and then stir to distribute it evenly in the aquarium.

Special precautions for storage

- Keep ektomor in a dry place out of direct light. Store in its original packaging.

- Keep out of reach of children.

Special warnings

- For ornamental fish. Do not use on creatures which are used to obtain human food.
- Do not use after the use-by date has expired.

Special precautions for the disposal of unused pharmaceuticals

Take unused medical products and unfinished containers of medical products to the designated collection points.